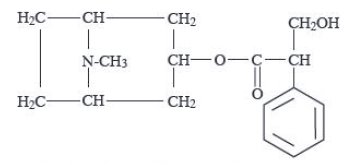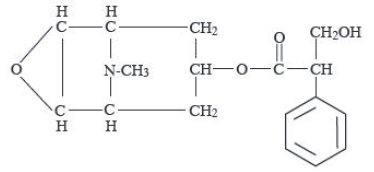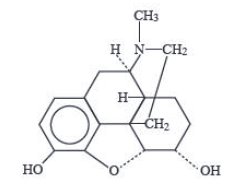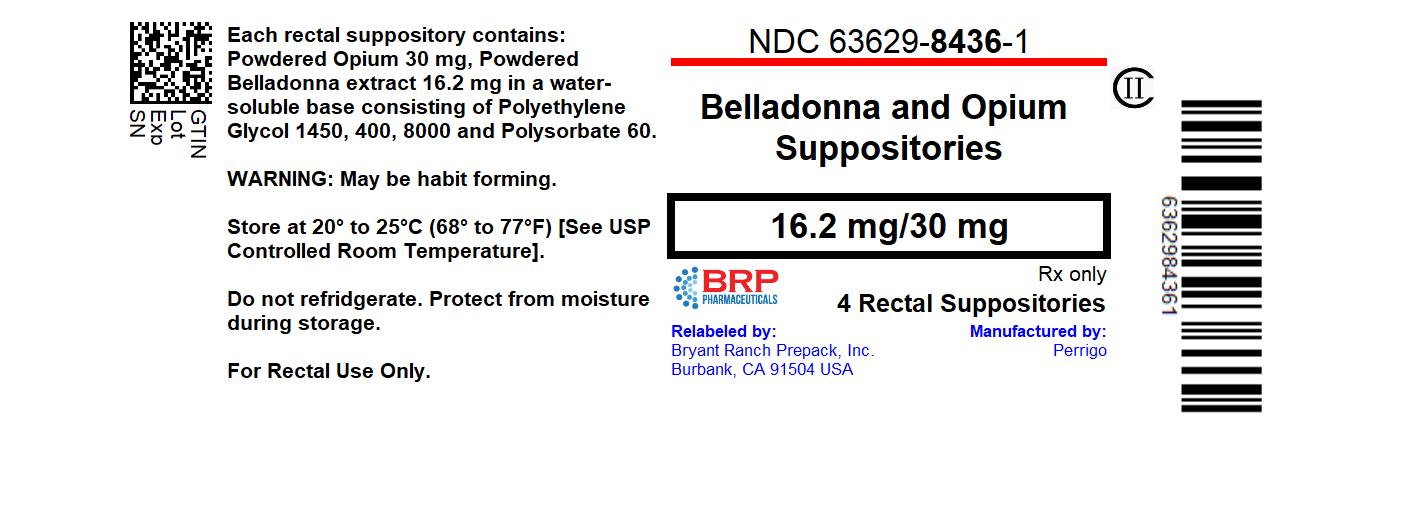 DRUG LABEL: Belladonna and Opium
NDC: 63629-8436 | Form: SUPPOSITORY
Manufacturer: Bryant Ranch Prepack
Category: prescription | Type: HUMAN PRESCRIPTION DRUG LABEL
Date: 20240111
DEA Schedule: CII

ACTIVE INGREDIENTS: ATROPA BELLADONNA 16.2 mg/1 1; OPIUM 30 mg/1 1
INACTIVE INGREDIENTS: POLYETHYLENE GLYCOL 400; POLYETHYLENE GLYCOL 8000; POLYETHYLENE GLYCOL 1450; POLYSORBATE 60

HIGHLIGHTS OF PRESCRIBING INFORMATION

These highlights do not include all the information needed to use BELLADONNA and OPIUM Suppositories safely and effectively. See full prescribing information for BELLADONNA and OPIUM Suppositories.
BELLADONNA and OPIUM Suppositories, for rectal use, CII
Initial U.S. Approval: 1938

WARNING: ADDICTION, ABOUSE, AND MISUSE; LIFE-THREATENING RESPIRATORY DEPRESSION; ACCIDENTAL EXPOSURE; NEONATAL OPIOD WITHDRAWAL SYNDROME; and RISKS FROM CONCOMITANT USE WITH ALCOHOL, BENZODIAZEPINES OR OTHER CNS DEPRESSANTS

See full prescribing information for complete boxed warning.

- Belladonna and opium suppositories expose users to risks of opioid addiction, abuse, and misuse, which can lead to overdose and death. Assess patient’s risk before prescribing and monitor regularly for these behaviors or conditions. (5.1)
- Serious, life-threatening, or fatal respiratory depression may occur. Monitor closely, especially upon initiation or following a dose increase. (5.2)
- Accidental exposure of belladonna and opium suppositories, especially by children, can result in a fatal overdose of opium. (5.2)
- Prolonged use of belladonna and opium suppositories during pregnancy can result in neonatal opioid withdrawal syndrome, which may be life-threatening if not recognized and treated. If prolonged opioid use is required in a pregnant woman, advise the patient of the risk of neonatal opioid withdrawal syndrome and ensure that appropriate treatment will be available. (5.3)
- Concomitant use of opioids with benzodiazepines or other central nervous system (CNS) depressants, including alcohol, may result in profound sedation, respiratory depression, coma, and death. Reserve concomitant prescribing for use in patients for whom alternative treatment options are inadequate; limit dosages and durations to the minimum required; and follow patients for signs and symptoms of respiratory depression and sedation. (5.4, 7)

RECENT MAJOR CHANGES

Boxed Warning | 12/2017
Indications and Usage (1) | 12/2017
Dosage and Administration (2) | 12/2017
Contraindications (4) | 12/2017
Warnings and Precautions (5) | 12/2017

1 INDICATIONS AND USAGE

Belladonna and opium suppositories are an opioid agonist indicated for the management of ureteral spasm pain severe enough to require an opioid analgesic and for which alternative treatments are inadequate.

Limitations of Use

Because of the risks of addiction, abuse, and misuse with opioids, even at recommended doses [see Warnings and Precautions (5.1)], reserve belladonna and opium suppositories for use in patients for whom alternative treatment options [e.g., non-opioid analgesics or opioid combination products]:

- Have not been tolerated, or are not expected to be tolerated,
- Have not provided adequate analgesia, or are not expected to provide adequate analgesia

2 DOSAGE AND ADMINISTRATION

- Use the lowest effective dosage for the shortest duration consistent with individual patient treatment goals. (2.1)
- Individualize dosing based on the severity of pain, patient response, and prior analgesic experience, and risk factor for addiction, abuse, and misuse. (2.1)
- Initiate dosing with one suppository once or twice daily as needed for pain. (2.2)
- Do not stop belladonna and opium suppositories abruptly in a physically dependent patient. (2.4)

3 DOSAGE FORMS AND STRENGTHS

Suppositories:

- Belladonna 16.2 mg and opium 30 mg
- Belladonna 16.2 mg and opium 60 mg

4 CONTRAINDICATIONS

- Significant respiratory depression. (4)
- Acute or severe bronchial asthma in an unmonitored setting or in absence of resuscitative equipment. (4)
- Concurrent use of monoamine oxidase inhibitors (MAOIs) or use of MAOIs within the last 14 days (4)
- Known or suspected gastrointestinal obstruction, including paralytic ileus. (4)
- Hypersensitivity to opium or belladonna. (4)

5 WARNINGS AND PRECAUTIONS

- Life-Threatening Respiratory Depression in Patients with Chronic Pulmonary Disease or in Elderly, Cachectic, or Debilitated Patients: Monitor closely, particularly during initiation and titration. (5.5)
- Adrenal Insufficiency: If diagnosed, treat with physiologic replacement of corticosteroids, and wean patient off of the opioid. (5.6)
- Severe Hypotension: Monitor during dosage initiation and titration. Avoid use of Morphine Sulfate Oral Solution in patients with circulatory shock. (5.7)
- Risks of Use in Patients with Increased Intracranial Pressure, Brain Tumors, Head Injury, or Impaired Consciousness: Monitor for sedation and respiratory depression. Avoid use of belladonna and opium suppositories in patients with impaired consciousness or coma. (5.8)

6 ADVERSE REACTIONS

Most common adverse reactions are drowsiness, dry mouth, urinary retention, photophobia, rapid pulse, dizziness and blurred vision, constipation, nausea and vomiting. (6)

To report SUSPECTED ADVERSE REACTIONS, contact Perrigo at 1-866-634-9120 or FDA at 1-800-FDA-1088 or www.fda.gov/medwatch.

7 DRUG INTERACTIONS

- Serotonergic Drugs: Concomitant use may result in serotonin syndrome. Discontinue belladonna and opium suppositories if serotonin syndrome is suspected. (7)
- Monoamine Oxidase Inhibitors (MAOIs): Can potentiate the effects of opium. Avoid concomitant use in patients receiving MAOIs or within 14 days of stopping treatment with an MAOI. (7)
- Mixed Agonist/Antagonist and Partial Agonist Opioid Analgesics: Avoid use with belladonna and opium suppositories because they may reduce analgesic effect of belladonna and opium suppositories or precipitate withdrawal symptoms. (7)

8 USE IN SPECIFIC POPULATIONS

Pregnancy: May cause fetal harm. (8.1)

Revised: 12/2017

FULL PRESCRIBING INFORMATION

WARNING: ADDICTION, ABOUSE, AND MISUSE; LIFE-THREATENING RESPIRATORY DEPRESSION; ACCIDENTAL EXPOSURE; NEONATAL OPIOD WITHDRAWAL SYNDROME; and RISKS FROM CONCOMITANT USE WITH ALCOHOL, BENZODIAZEPINES OR OTHER CNS DEPRESSANTS

Addiction, Abuse, and Misuse

Belladonna and opium suppositories expose patients and other users to the risks of opioid addiction, abuse, and misuse, which can lead to overdose and death. Assess each patient’s risk prior to prescribing belladonna and opium suppositories, and monitor all patients regularly for the development of these behaviors or conditions [see Warnings and Precautions (5.1)].

Life-Threatening Respiratory Depression

Serious, life-threatening, or fatal respiratory depression may occur with use of belladonna and opium suppositories. Monitor for respiratory depression, especially during initiation of belladonna and opium suppositories or following a dose increase [see Warnings and Precautions (5.2)].

Accidental Exposure

Accidental exposure of even one dose of belladonna and opium suppositories, especially by children, can result in a fatal overdose of opium [see Warnings and Precautions (5.2)].

Neonatal Opioid Withdrawal Syndrome

Prolonged use of belladonna and opium suppositories during pregnancy can result in neonatal opioid withdrawal syndrome, which may be life-threatening if not recognized and treated, and requires management according to protocols developed by neonatology experts. If opioid use is required for a prolonged period in a pregnant woman, advise the patient of the risk of neonatal opioid withdrawal syndrome and ensure that appropriate treatment will be available [see Warnings and Precautions (5.3)].

Risks From Concomitant Use With Alcohol, Benzodiazepines Or Other CNS Depressants

Concomitant use of opioids with benzodiazepines or other central nervous system (CNS) depressants, including alcohol, may result in profound sedation, respiratory depression, coma, and death [see Warnings and Precautions (5.4), Drug Interactions (7)].

- Reserve concomitant prescribing of belladonna and opium suppositories and benzodiazepines or other CNS depressants for use in patients for whom alternative treatment options are inadequate.
- Limit dosages and durations to the minimum required.
- Follow patients for signs and symptoms of respiratory depression and sedation

1 INDICATIONS AND USAGE

Belladonna and opium suppositories are indicated for the management of ureteral spasm pain severe enough to require an opioid analgesic and for which alternative treatments are inadequate.

Limitations of Use

Because of the risks of addiction, abuse, and misuse with opioids, even at recommended doses [see Warnings and Precautions (5.1)], reserve belladonna and opium suppositories for use in patients for whom alternative treatment options [e.g., non-opioid analgesics or opioid combination products]:

- Have not been tolerated, or are not expected to be tolerated,
- Have not provided adequate analgesia, or are not expected to provide adequate analgesic

2 DOSAGE AND ADMINISTRATION

2.1 Important Dosage and Administration Instructions

Use the lowest effective dosage for the shortest duration consistent with individual patient treatment goals [see Warnings and Precautions (5)].

Initiate the dosing regimen for each patient individually, taking into account the patient's severity of pain, patient response, prior analgesic treatment experience, and risk factors for addiction, abuse, and misuse [see Warnings and Precautions (5.1)].

Monitor patients closely for respiratory depression, especially within the first 24-72 hours of initiating therapy and following dosage increases with belladonna and opium suppositories and adjust the dosage accordingly [see Warnings and Precautions (5.2)].

2.2 Dosing

One belladonna and opium suppository rectally once or twice daily, not to exceed four doses daily or as recommended by the physician. Moisten finger and suppository with water before inserting. Absorption is dependent on body hydration and not on body temperature. Not recommended for use in children 12 years of age and under.

Conversion from Other Opioids to Belladonna and Opium Suppositories

There is inter-patient variability in the potency of opioid drugs and opioid formulations. Therefore, a conservative approach is advised when determining the total daily dosage of belladonna and opium suppositories. It is safer to underestimate a patient’s 24-hour belladonna and opium suppositories dosage than to overestimate the 24-hour belladonna and opium suppositories dosage and manage an adverse reaction due to overdose.

Conversion from Belladonna and Opium suppositories to Extended-Release Opioid

The relative bioavailability of belladonna and opium suppositories compared to extended-release opioid is unknown, so conversion to extended-release drug product must be accompanied by close observation for signs of excessive sedation and respiratory depression.

2.3 Maintenance of Therapy

Continually reevaluate patients receiving belladonna and opium suppositories to assess the maintenance of pain control and the relative incidence of adverse reactions, as well as monitoring for the development of addiction, abuse, or misuse [see Warnings and Precautions (5.1)]. Frequent communication is important among the prescriber, other members of the healthcare team, the patient, and the caregiver/family during periods of changing analgesic requirements, including initial titration.

If the level of pain increases after dosage stabilization, attempt to identify the source of increased pain before increasing the belladonna and opium suppositories dosage. If unacceptable opioid-related adverse reactions are observed, consider reducing the dosage. Adjust the dosage to obtain an appropriate balance between management of pain and opioid-related adverse reactions.

2.4 Discontinuation of Belladonna and Opium Suppositories

When a patient who has been taking belladonna and opium suppositories regularly and may be physically dependent no longer requires therapy with belladonna and opium suppositories, use a gradual downward titration of the dosage to prevent signs and symptoms of withdrawal. Do not stop belladonna and opium suppositories abruptly [see Warnings and Precautions (5.12), Drug Abuse and Dependence (9.3)].

3 DOSAGE FORMS AND STRENGTHS

Belladonna and Opium Suppositories are available in two strengths.

- Belladonna 16.2 mg and opium 30 mg
- Belladonna 16.2 mg and opium 60 mg

4 CONTRAINDICATIONS

- Belladonna and opium suppositories are contraindicated in patients with:
- Significant respiratory depression [see Warnings and Precautions (5.2)]
- Acute or severe bronchial asthma in an unmonitored setting or in the absence of resuscitative equipment [see Warnings and Precautions (5.5)]
- Concurrent use of monoamine oxidase inhibitors (MAOIs) or use of MAOIs within the last 14 days [see Warnings and Precautions (5.7), Drug Interactions (7)]
- Known or suspected gastrointestinal obstruction, including paralytic ileus [see Warnings and Precautions (5.9)]
- Hypersensitivity to opium or belladonna [see Adverse Events (6)]
- Glaucoma^2
- Severe hepatic or renal disease^2
- Narcotic idiosyncrasies^2
- Convulsive disorders^2
- Acute alcoholism^2
- Delirium tremens^2
- Premature labor^2

5 WARNINGS AND PRECAUTIONS

These preparations are not recommended for use in children.

5.1 Addiction, Abuse, and Misuse

Belladonna and opium suppositories contains opium, a Schedule II controlled substance. As an opioid, belladonna and opium suppositories exposes users to the risks of addiction, abuse, and misuse [see Drug Abuse and Dependence (9)].

Although the risk of addiction in any individual is unknown, it can occur in patients appropriately prescribed belladonna and opium suppositories. Addiction can occur at recommended dosages and if the drug is misused or abused.

Assess each patient’s risk for opioid addiction, abuse, or misuse prior to prescribing belladonna and opium suppositories, and monitor all patients receiving belladonna and opium suppositories for the development of these behaviors or conditions. Risks are increased in patients with a personal or family history of substance abuse (including drug or alcohol abuse or addiction) or mental illness (e.g., major depression). The potential for these risks should not, however, prevent the proper management of pain in any given patient. Patients at increased risk may be prescribed opioids such as belladonna and opium suppositories, but use in such patients necessitates intensive counseling about the risks and proper use of belladonna and opium suppositories along with intensive monitoring for signs of addiction, abuse, and misuse.

Opioids are sought by drug abusers and people with addiction disorders and are subject to criminal diversion. Consider these risks when prescribing or dispensing belladonna and opium suppositories. Strategies to reduce these risks include prescribing the drug in the smallest appropriate quantity and advising the patient on the proper disposal of unused drug [see Patient Counseling Information (17)]. Contact local state professional licensing board or state controlled substances authority for information on how to prevent and detect abuse or diversion of this product.

5.2 Life-Threatening Respiratory Depression

Serious, life-threatening, or fatal respiratory depression has been reported with the use of opioids, even when used as recommended. Respiratory depression, if not immediately recognized and treated, may lead to respiratory arrest and death. Management of respiratory depression may include close observation, supportive measures, and use of opioid antagonists, depending on the patient’s clinical status [see Overdosage (10)]. Carbon dioxide (CO2) retention from opioid-induced respiratory depression can exacerbate the sedating effects of opioids.

While serious, life-threatening, or fatal respiratory depression can occur at any time during the use of belladonna and opium suppositories, the risk is greatest during the initiation of therapy or following a dosage increase. Monitor patients closely for respiratory depression, especially within the first 24-72 hours of initiating therapy with and following dosage increases of belladonna and opium suppositories.

To reduce the risk of respiratory depression, proper dosing of belladonna and opium suppositories is essential [see Dosage and Administration (2.2)]. Overestimating the belladonna and opium suppositories dosage when converting patients from another opioid product can result in a fatal overdose with the first dose.

Accidental exposure of even one dose of belladonna and opium suppositories, especially by children, can result in respiratory depression and death due to an overdose of opium.

5.3 Neonatal Opioid Withdrawal Syndrome

Prolonged use of belladonna and opium suppositories during pregnancy can result in withdrawal in the neonate. Neonatal opioid withdrawal syndrome, unlike opioid withdrawal syndrome in adults, may be life-threatening if not recognized and treated, and requires management according to protocols developed by neonatology experts. If opioid use is required for a prolonged period in a pregnant woman, advise the patient of the risk of neonatal opioid withdrawal syndrome and ensure that appropriate treatment will be available [see Use in Specific Populations (8.1), Patient Counseling Information].

5.4 Risks from Concomitant Use with Alcohol, Benzodiazepines or Other Central Nervous System Depressants

Profound sedation, respiratory depression, coma, and death may result from the concomitant use of belladonna and opium suppositories with benzodiazepines or other CNS depressants (e.g., non-benzodiazepine sedatives/hypnotics, anxiolytics, tranquilizers, muscle relaxants, general anesthetics, antipsychotics, other opioids, alcohol). Because of these risks, reserve concomitant prescribing of these drugs for use in patients for whom alternative treatment options are inadequate.

Observational studies have demonstrated that concomitant use of opioid analgesics and benzodiazepines increases the risk of drug-related mortality compared to use of opioid analgesics alone. Because of similar pharmacological properties, it is reasonable to expect similar risk with the concomitant use of other CNS depressant drugs with opioid analgesics [see Drug Interactions (7)].

If the decision is made to prescribe a benzodiazepine or other CNS depressant concomitantly with an opioid analgesic, prescribe the lowest effective dosages and minimum durations of concomitant use. In patients already receiving an opioid analgesic, prescribe a lower initial dose of the benzodiazepine or other CNS depressant than indicated in the absence of an opioid, and titrate based on clinical response. If an opioid analgesic is initiated in a patient already taking a benzodiazepine or other CNS depressant, prescribe a lower initial dose of the opioid analgesic, and titrate based on clinical response. Follow patients closely for signs and symptoms of respiratory depression and sedation.

Advise both patients and caregivers about the risks of respiratory depression and sedation when belladonna and opium suppositories are used with benzodiazepines or other CNS depressants (including alcohol and illicit drugs). Advise patients not to drive or operate heavy machinery until the effects of concomitant use of the benzodiazepine or other CNS depressant have been determined. Screen patients for risk of substance use disorders, including opioid abuse and misuse, and warn them of the risk for overdose and death associated with the use of additional CNS depressants including alcohol and illicit drugs [see Drug Interactions (7) and Patient Counseling Information (17)].

5.5 Life-Threatening Respiratory Depression in Patients with Chronic Pulmonary Disease or in Elderly, Cachectic, or Debilitated Patients

The use of belladonna and opium suppositories in patients with acute or severe bronchial asthma in an unmonitored setting or in the absence of resuscitative equipment is contraindicated.

Patients with Chronic Pulmonary Disease: belladonna and opium suppositories-treated patients with significant chronic obstructive pulmonary disease or cor pulmonale, and those with a substantially decreased respiratory reserve, hypoxia, hypercapnia, or pre-existing respiratory depression are at increased risk of decreased respiratory drive including apnea, even at recommended dosages of belladonna and opium suppositories [see Warnings and Precautions (5.2)].

Elderly, Cachetic, or Debilitated Patients: Life-threatening respiratory depression is more likely to occur in elderly, cachectic, or debilitated patients because they may have altered pharmacokinetics or altered clearance compared to younger, healthier patients [see Warnings and Precautions (5.2)].

Monitor such patients closely, particularly when initiating and titrating belladonna and opium suppositories and when belladonna and opium suppositories is given concomitantly with other drugs that depress respiration [see Warnings and Precautions (5.2)]. Alternatively, consider the use of non-opioid analgesics in these patients.

5.6 Interactions with Monoamine Oxidase Inhibitors

Monoamine oxidase inhibitors (MAOIs) may potentiate the effects of opioids, including respiratory depression, coma, and confusion. Belladonna and Opium Suppositories should not be used in patients taking MAOIs or within 14 days of stopping such treatment.

5.7 Adrenal Insufficiency

Cases of adrenal insufficiency have been reported with opioid use, more often following greater than one month of use. Presentation of adrenal insufficiency may include non-specific symptoms and signs including nausea, vomiting, anorexia, fatigue, weakness, dizziness, and low blood pressure. If adrenal insufficiency is suspected, confirm the diagnosis with diagnostic testing as soon as possible. If adrenal insufficiency is diagnosed, treat with physiologic replacement doses of corticosteroids. Wean the patient off of the opioid to allow adrenal function to recover and continue corticosteroid treatment until adrenal function recovers. Other opioids may be tried as some cases reported use of a different opioid without recurrence of adrenal insufficiency. The information available does not identify any particular opioids as being more likely to be associated with adrenal insufficiency.

5.8 Severe Hypotension

Belladonna and opium suppositories may cause severe hypotension including orthostatic hypotension and syncope in ambulatory patients. There is increased risk in patients whose ability to maintain blood pressure has already been compromised by a reduced blood volume or concurrent administration of certain CNS depressant drugs (e.g., phenothiazines or general anesthetics) [see Drug Interactions (7)]. Monitor these patients for signs of hypotension after initiating or titrating the dosage of belladonna and opium suppositories. In patients with circulatory shock, belladonna and opium suppositories may cause vasodilation that can further reduce cardiac output and blood pressure. Avoid the use of belladonna and opium suppositories in patients with circulatory shock.

5.9 Risks of Use in Patients with Increased Intracranial Pressure, Brain Tumors, Head Injury, or Impaired Consciousness

In patients who may be susceptible to the intracranial effects of CO2 retention (e.g., those with evidence of increased intracranial pressure or brain tumors), belladonna and opium suppositories may reduce respiratory drive, and the resultant CO2 retention can further increase intracranial pressure. Monitor such patients for signs of sedation and respiratory depression, particularly when initiating therapy with belladonna and opium suppositories.

Opioids may also obscure the clinical course in a patient with a head injury. Avoid the use of belladonna and opium suppositories in patients with impaired consciousness or coma.

5.10 Risks of Use in Patients with Gastrointestinal Conditions

Belladonna and opium suppositories are contraindicated in patients with known or suspected gastrointestinal obstruction, including paralytic ileus.

The opium in belladonna and opium suppositories may cause spasm of the sphincter of Oddi. Opioids may cause increases in serum amylase. Monitor patients with biliary tract disease, including acute pancreatitis, for worsening symptoms.

5.11 Increased Risk of Seizures in Patients with Seizure Disorders

The opium in belladonna and opium suppositories may increase the frequency of seizures in patients with seizure disorders, and may increase the risk of seizures occurring in other clinical settings associated with seizures. Monitor patients with a history of seizure disorders for worsened seizure control during belladonna and opium suppositories therapy.

5.12 Withdrawal

Avoid the use of mixed agonist/antagonist (e.g., pentazocine, nalbuphine, and butorphanol) or partial agonist (e.g., buprenorphine) analgesics in patients who are receiving a full opioid agonist analgesic, including belladonna and opium suppositories. In these patients, mixed agonist/antagonist and partial agonist analgesics may reduce the analgesic effect and/or precipitate withdrawal symptoms [see Drug Interactions (7)].

When discontinuing belladonna and opium suppositories, gradually taper the dosage [see Dosage and Administration (2.4)].

Do not abruptly discontinue belladonna and opium suppositories [see Drug Abuse and Dependence (9.3)].

5.13 Risks of Driving and Operating Machinery

Belladonna and opium suppositories may impair the mental or physical abilities needed to perform potentially hazardous activities such as driving a car or operating machinery. Warn patients not to drive or operate dangerous machinery unless they are tolerant to the effects of belladonna and opium suppositories and know how they will react to the medication [see Patient Counseling Information (17)].

6 ADVERSE REACTIONS

Belladonna may cause drowsiness, dry mouth, urinary retention, photophobia, rapid pulse, dizziness and blurred vision^7. Opium usage may result in constipation, nausea or vomiting. Pruritis and urticaria may occasionally occur. Hypersensitivity to opium or belladonna may occur.

The following serious adverse reactions are described, or described in greater detail, in other sections:

- Addiction, Abuse, and Misuse [see Warnings and Precautions (5.1)]
- Life-Threatening Respiratory Depression [see Warnings and Precautions (5.2)]
- Neonatal Opioid Withdrawal Syndrome [see Warnings and Precautions (5.3)]
- Interactions with Benzodiazepines and Other CNS Depressants [see Warnings and Precautions (5.4)]
- Adrenal Insufficiency [see Warnings and Precautions (5.6)]
- Severe Hypotension [see Warnings and Precautions (5.7)]
- Gastrointestinal Adverse Reactions [see Warnings and Precautions (5.9)]
- Seizures [see Warnings and Precautions (5.11)]
- Withdrawal [see Warnings and Precautions (5.12)]

6.2 Postmarketing Experience

The following adverse reactions have been identified during post-approval use of opioids. Because these reactions are reported voluntarily from a population of uncertain size, it is not always possible to reliably estimate their frequency or establish a causal relationship to drug exposure.

Serotonin syndrome: Cases of serotonin syndrome, a potentially life-threatening condition, have been reported during concomitant use of opioids with serotonergic drugs.

Adrenal insufficiency: Cases of adrenal insufficiency have been reported with opioid use, more often following greater than one month of use.

Anaphylaxis: Anaphylaxis has been reported with products containing opioids.

Androgen deficiency: Cases of androgen deficiency have occurred with chronic use of opioids

7 DRUG INTERACTIONS

Table 1 includes clinically significant drug interactions with belladonna and opium suppositories.

Table 1: Clinically Significant Drug Interactions with Belladonna and Opium Suppositories

Alcohol, Benzodiazepines and Other Central Nervous System (CNS) Depressants
Clinical Impact: | Due to additive pharmacologic effect, the concomitant use of benzodiazepines or other CNS depressants, including alcohol, can increase the risk of hypotension, respiratory depression, profound sedation, coma, and death.
Intervention: | Reserve concomitant prescribing of these drugs for use in patients for whom alternative treatment options are inadequate. Limit dosages and durations to the minimum required. Follow patients closely for signs of respiratory depression and sedation [see Warnings and Precautions (5.4)].
Examples: | Benzodiazepines and other sedatives/hypnotics, anxiolytics, tranquilizers, muscle relaxants, general anesthetics, antipsychotics, other opioids, alcohol.
Serotonergic Drugs
Clinical Impact: | The concomitant use of opioids with other drugs that affect the serotonergic neurotransmitter system has resulted in serotonin syndrome.
Intervention: | If concomitant use is warranted, carefully observe the patient, particularly during treatment initiation and dose adjustment. Discontinue belladonna and opium suppositories if serotonin syndrome is suspected.
Examples: | Selective serotonin reuptake inhibitors (SSRIs), serotonin and norepinephrine reuptake inhibitors (SNRIs), tricyclic antidepressants (TCAs), triptans, 5-HT3 receptor antagonists, drugs that effect the serotonin neurotransmitter system (e.g., mirtazapine, trazodone, tramadol), monoamine oxidase (MAOI) inhibitors (those intended to treat psychiatric disorders and also others, such as linezolid and intravenous methylene blue).
Monoamine Oxidase Inhibitors (MAOIs)
Clinical Impact: | MAOI interactions with opioids may manifest as serotonin syndrome or opioid toxicity (e.g., respiratory depression, coma) [see Warnings and Precautions (5.2)]; If urgent use of an opioid is necessary, use test doses and frequent titration of small doses to treat pain while closely monitoring blood pressure and signs and symptoms of CNS and respiratory depression.
Intervention: | The use of belladonna and opium suppositories is not recommended for patients taking MAOIs or within 14 days of stopping such treatment.
Examples: | phenelzine, tranylcypromine, linezolid
Mixed Agonist/Antagonist and Partial Agonist Opioid Analgesics
Clinical Impact: | May reduce the analgesic effect of belladonna and opium suppositories and/or precipitate withdrawal symptoms.
Intervention: | Avoid concomitant use.
Examples: | butorphanol, nalbuphine, pentazocine, buprenorphine
Muscle Relaxants
Clinical Impact: | Opium may enhance the neuromuscular blocking action of skeletal muscle relaxants and produce an increased degree of respiratory depression.
Intervention: | Monitor patients for signs of respiratory depression that may be greater than otherwise expected and decrease the dosage of belladonna and opium suppositories and/or the muscle relaxant as necessary.
Diuretics
Clinical Impact: | Opioids can reduce the efficacy of diuretics by inducing the release of antidiuretic hormone.
Intervention: | Monitor patients for signs of diminished diuresis and/or effects on blood pressure and increase the dosage of the diuretic as needed.
Anticholinergic Drugs
Clinical Impact: | The concomitant use of anticholinergic drugs may increase risk of urinary retention and/or severe constipation, which may lead to paralytic ileus.
Intervention: | Monitor patients for signs of urinary retention or reduced gastric motility when belladonna and opium suppositories are used concomitantly with anticholinergic drugs.

8 USE IN SPECIFIC POPULATIONS

8.1 Pregnancy

Risk Summary

Prolonged use of opioid analgesics during pregnancy may cause neonatal opioid withdrawal syndrome. There are no available data with belladonna and opium suppositories in pregnant women to inform a drug associated risk for major birth defects and miscarriage.

Clinical Considerations

Fetal/Neonatal Adverse Reactions

Prolonged use of opioid analgesics during pregnancy for medical or nonmedical purposes can result in physical dependence in the neonate and neonatal opioid withdrawal syndrome shortly after birth.

Neonatal opioid withdrawal syndrome presents as irritability, hyperactivity and abnormal sleep pattern, high pitched cry, tremor, vomiting, diarrhea and failure to gain weight. The onset, duration, and severity of neonatal opioid withdrawal syndrome vary based on the specific opioid used, duration of use, timing and amount of last maternal use, and rate of elimination of the drug by the newborn. Observe newborns for symptoms of neonatal opioid withdrawal syndrome and manage accordingly [see Warnings and Precautions (5.3)].

Belladonna refers to plant alkaloids that contain anticholinergic agents such as atropine. Atropine used in human pregnancies has not been associated with birth defects or adverse fetal effects although the drug readily crosses the placenta. Use during pregnancy may increase risk of respiratory abnormalities, hypospadias, and eye or ear malformations but causal relationship is unclear. The Collaborative Perinatal Project found no relationship between first trimester use of atropine and birth defects in the offspring but found an increase in birth defects in general in the offspring of pregnancies where the mother had taken belladonna. There was no relationship to any particular syndrome of anomalies. A statistically significant (although weak) association was discovered between congenital anomalies and maternal use of belladonna. A study was conducted based on the infants of 554 women who took belladonna during the first four months of pregnancy. The study was conducted in the Collaborative Perinatal Project and showed that belladonna is unlikely to cause minor congenital abnormalities. The estimated maximum risk is most likely less than 3% if maternal belladonna is used early in pregnancy.^1

Labor or Delivery

Opioids cross the placenta and may produce respiratory depression and psycho-physiologic effects in neonates. An opioid antagonist, such as naloxone, must be available for reversal of opioid-induced respiratory depression in the neonate. Belladonna and opium suppositories is not recommended for use in pregnant women during or immediately prior to labor, when other analgesic techniques are more appropriate. Opioid analgesics, including belladonna and opium suppositories, can prolong labor through actions which temporarily reduce the strength, duration, and frequency of uterine contractions. However, this effect is not consistent and may be offset by an increased rate of cervical dilation, which tends to shorten labor. Monitor neonates exposed to opioid analgesics during labor for signs of excess sedation and respiratory depression.

8.2 Lactation

Risk Summary

The developmental and health benefits of breastfeeding should be considered along with the mother’s clinical need for belladonna and opium suppositories and any potential adverse effects on the breastfed infant from belladonna and opium suppositories or from the underlying maternal condition.

Clinical Considerations

Infants exposed to belladonna and opium suppositories through breast milk should be monitored for excess sedation and respiratory depression. Withdrawal symptoms can occur in breastfed infants when maternal administration of an opioid analgesic is stopped, or when breast-feeding is stopped.

8.3 Females and Males of Reproductive Potential

Infertility

Chronic use of opioids may cause reduced fertility in females and males of reproductive potential. It is not known whether these effects on fertility are reversible [see Adverse Reactions (6.1)].

8.4 Pediatric Use

The safety and effectiveness of belladonna and opium suppositories in pediatric patients have not been established.

8.5 Geriatric Use

Elderly patients (aged 65 years or older) may have increased sensitivity to belladonna and opium. In general, use caution when selecting a dosage for an elderly patient, usually starting at the low end of the dosing range, reflecting the greater frequency of decreased hepatic, renal, or cardiac function and of concomitant disease or other drug therapy.

Respiratory depression is the chief risk for elderly patients treated with opioids, and has occurred after large initial doses were administered to patients who were not opioid-tolerant or when opioids were co-administered with other agents that depress respiration. Titrate the dosage of belladonna and opium suppositories slowly in geriatric patients [see Warnings and Precautions (5.2)].

9 DRUG ABUSE AND DEPENDENCE

9.1 Controlled Substance

Belladonna and opium suppositories contains opium, a Schedule II controlled substance.

9.2 Abuse

Belladonna and opium suppositories contains opium, a substance with a high potential for abuse similar to other opioids including fentanyl, hydrocodone, hydromorphone, methadone, morphine, oxycodone, oxymorphone, and tapentadol. Belladonna and opium suppositories can be abused and is subject to misuse, addiction, and criminal diversion [see Warnings and Precautions (5.1)].

All patients treated with opioids require careful monitoring for signs of abuse and addiction, since use of opioid analgesic products carries the risk of addiction even under appropriate medical use.

Prescription drug abuse is the intentional non-therapeutic use of a prescription drug, even once, for its rewarding psychological or physiological effects.

Drug addiction is a cluster of behavioral, cognitive, and physiological phenomena that develop after repeated substance use and includes: a strong desire to take the drug, difficulties in controlling its use, persisting in its use despite harmful consequences, a higher priority given to drug use than to other activities and obligations, increased tolerance, and sometimes a physical withdrawal.

“Drug-seeking” behavior is very common in persons with substance use disorders. Drug-seeking tactics include emergency calls or visits near the end of office hours, refusal to undergo appropriate examination, testing, or referral, repeated “loss” of prescriptions, tampering with prescriptions and reluctance to provide prior medical records or contact information for other treating health care provider(s). “Doctor shopping” (visiting multiple prescribers) to obtain additional prescriptions is common among drug abusers and people suffering from untreated addiction. Preoccupation with achieving adequate pain relief can be appropriate behavior in a patient with poor pain control.

Abuse and addiction are separate and distinct from physical dependence and tolerance. Health care providers should be aware that addiction may not be accompanied by concurrent tolerance and symptoms of physical dependence in all addicts. In addition, abuse of opioids can occur in the absence of true addiction.

Belladonna and opium suppositories, like other opioids, can be diverted for non-medical use into illicit channels of distribution. Careful record-keeping of prescribing information, including quantity, frequency, and renewal requests, as required by state and federal law, is strongly advised.

Proper assessment of the patient, proper prescribing practices, periodic re-evaluation of therapy, and proper dispensing and storage are appropriate measures that help to limit abuse of opioid drugs.

Risks Specific to Abuse of Belladonna and Opium Suppositories

Belladonna and opium suppositories are for rectal use only. Abuse of belladonna and opium suppositories poses a risk of overdose and death. The risk is increased with concurrent abuse of belladonna and opium suppositories with alcohol and other central nervous system depressants.

Parenteral drug abuse is commonly associated with transmission of infectious diseases such as hepatitis and HIV.

9.3 Dependence

Both tolerance and physical dependence can develop during chronic opioid therapy. Tolerance is the need for increasing doses of opioids to maintain a defined effect such as analgesia (in the absence of disease progression or other external factors). Tolerance may occur to both the desired and undesired effects of drugs, and may develop at different rates for different effects.

Physical dependence results in withdrawal symptoms after abrupt discontinuation or a significant dosage reduction of a drug. Withdrawal also may be precipitated through the administration of drugs with opioid antagonist activity (e.g., naloxone, nalmefene), mixed agonist/antagonist analgesics (pentazocine, butorphanol, nalbuphine), or partial agonists (buprenorphine). Physical dependence may not occur to a clinically significant degree until after several days to weeks of continued opioid usage.

Belladonna and opium suppositories should not be abruptly discontinued [see Dosage and Administration (2.4)]. If belladonna and opium suppositories is abruptly discontinued in a physically-dependent patient, a withdrawal syndrome may occur. Some or all of the following can characterize this syndrome: restlessness, lacrimation, rhinorrhea, yawning, perspiration, chills, myalgia, and mydriasis. Other signs and symptoms also may develop, including: irritability, anxiety, backache, joint pain, weakness, abdominal cramps, insomnia, nausea, anorexia, vomiting, diarrhea, or increased blood pressure, respiratory rate, or heart rate.

Infants born to mothers physically dependent on opioids will also be physically dependent and may exhibit respiratory difficulties and withdrawal signs [see Use in Specific Populations (8.1)].

10 OVERDOSAGE

Clinical Presentation

Acute overdose with belladonna and opium suppositories can be manifested by respiratory depression, somnolence progressing to stupor or coma, skeletal muscle flaccidity, cold and clammy skin, constricted pupils, and, in some cases, pulmonary edema, bradycardia, hypotension, partial or complete airway obstruction, atypical snoring, and death. Marked mydriasis rather than miosis may be seen with hypoxia in overdose situations [see Clinical Pharmacology (12)].

Treatment of Overdose

In case of overdose, priorities are the reestablishment of a patent and protected airway and institution of assisted or controlled ventilation, if needed. Employ other supportive measures (including oxygen and vasopressors) in the management of circulatory shock and pulmonary edema as indicated. Cardiac arrest or arrhythmias will require advanced life-support techniques.

The opioid antagonists, naloxone or nalmefene, are specific antidotes to respiratory depression resulting from opioid overdose. For clinically significant respiratory or circulatory depression secondary to opium overdose, administer an opioid antagonist. Opioid antagonists should not be administered in the absence of clinically significant respiratory or circulatory depression secondary to opium overdose.

Because the duration of opioid reversal is expected to be less than the duration of action of opium in belladonna and opium suppositories, carefully monitor the patient until spontaneous respiration is reliably re-established. If the response to an opioid antagonist is suboptimal or only brief in nature, administer additional antagonist as directed by the product’s prescribing information.

11 DESCRIPTION

Each belladonna and opium suppository contains (in a water-soluble base consisting of polyethylene glycol 400, 1450, 8000 and polysorbate 60):

Belladonna (16.2 mg) and Opium (30 mg):

Powdered belladonna extract 16.2 mg and powdered opium 30 mg (Warning: May be habit forming).

Belladonna (16.2 mg) and Opium (60 mg):

Powdered belladonna extract 16.2 mg and powdered opium 60 mg (Warning: May be habit forming).

This drug falls into the pharmacological/therapeutic class of narcotic analgesic/antispasmotic agents.

The pharmacologically active principles present in the belladonna extract component of belladonna and opium suppositories are:

Established Name: Atropine

Chemical Name: dl Tropyl Tropate

Established Name: Scopolamine

Chemical Name: dl Scopolamine

Opium contains more than twenty alkaloids, the principle ones being morphine (10%), narcotine (6%), papaverine (1%) and codeine (0.5%). The major pharmacologically active principle of the powdered opium component of belladonna and opium suppositories, however, is:

Name: Morphine

Chemical Name: 7, 8-Didehydro-4, 5-epoxy-17-Methyl-morphinan-3, 6-diol

12 CLINICAL PHARMACOLOGY

12.1 Mechanism of Action

Belladonna/opium rectal suppository is a combination narcotic analgesic/antispasmodic agent. The belladonna extract component of the rectal suppository provides the active alkaloids atropine and scopolamine, while the opium component provides primarily morphine (among more than 20 alkaloids). The atropine alkaloid is parasympatholytic, exerting antispasmodic activity by relaxation of smooth muscle that is stimulated by the parasympathetic nervous system. The atropine alkaloid is also the dl isomer of l-hyoscyamine and exerts the same pharmacologic activity; however, it exerts about one-half the activity peripherally as l-hyoscyamine. Atropine activity also counteracts morphine induced smooth muscle spasm without affecting the analgesia. The morphine alkaloid of opium exerts analgesic activity by increasing the pain threshold and decreasing the sensitivity to pain. The oxidative dealkylated nor-metabolites of morphine begin the analgesic process. Additionally, the side effect of euphoria may contribute to sense of pain relief.

12.2 Pharmacodynamics

Through its parasympatholytic action, atropine (belladonna) relaxes smooth muscle resulting from parasympathetic stimulation. It is the dl isomer of l-hyoscyamine and therefore exhibits the same clinical effects. It is, however, approximately one-half as active peripherally as l-hyoscyamine, the latter being the major active plant alkaloid. The dl isomer atropine is formed during the process of isolation of the belladonna extract.^1

Morphine, the major active principle of powdered opium, is responsible for the action of powdered opium although the other alkaloids present also contribute to it. The sedative and analgesic action of morphine, the effect desired by inclusion in belladonna and opium suppositories of powdered opium, are thought to be due to the depressant effect on the cerebral cortex, hypothalamus and medullary centers. In large doses, the opiates and their analogs also exhibit synaptic conduction in the spinothalamic tracts, depress the function of the reticular formation, the lemniscus and the thalamic relays, and inhibit spinal synaptic reflexes: but these inhibitor actions should not be elicited with therapeutic doses of the drug. Moderate doses of powdered opium should not alter the electroencephalogram.

The action of morphine consists mainly of a descending depression of the central nervous system. It exerts its analgesic action by increasing the pain threshold or the magnitude of stimulus required to evoke pain and by dulling the sensibility or reaction to pain. In addition to its action in abolishing pain, morphine induces a sense of well-being (euphoria) facilitating certain mental processes while retarding others.

12.3 Pharmacokinetics

Upon absorption of morphine, oxidative dealkylation to produce nor-compounds appears to be the first step in the reaction sequence which imparts analgesia. Morphine is conjugated in the liver to form the 3-glucuronide which passes into the bile and is reabsorbed and excreted in the urine. The atropine effect of the belladonna extract serves to eliminate morphine induced smooth muscle spasm without affecting the sedative analgesic action of powdered opium.^1

15 REFERENCES

- Belladonna. DrugPoints Summary. Micromedex 2.0. Truven Health Analytics, Inc. Greenwood Village, CO. Accessed October 2, 2017.
- Olin BR. Drug Facts and Comparisons, 50th ed. Facts and Comparisons, St Louis, MO; 1999.

16 HOW SUPPLIED/STORAGE AND HANDLING

Belladonna (16.2 mg) and Opium (30 mg) suppositories are brown, bullet shaped suppositories.

NDC 63629-8436-1: Carton of 4 suppositories

Store at 20° to 25°C (68° to 77°F) [see USP Controlled Room Temperature]. DO NOT REFRIGERATE. PROTECT FROM MOISTURE DURING STORAGE.

Rx Only

17 PATIENT COUNSELING INFORMATION

Addiction, Abuse, and Misuse

Inform patients that the use of belladonna and opium suppositories, even when taken as recommended, can result in addiction, abuse, and misuse, which can lead to overdose and death [see Warnings and Precautions (5.1)]. Instruct patients not to share belladonna and opium suppositories with others and to take steps to protect belladonna and opium suppositories from theft or misuse.

Life-Threatening Respiratory Depression

Inform patients of the risk of life-threatening respiratory depression, including information that the risk is greatest when starting belladonna and opium suppositories or when the dosage is increased, and that it can occur even at recommended dosages [see Warnings and Precautions (5.2)]. Advise patients how to recognize respiratory depression and to seek medical attention if breathing difficulties develop.

Accidental Exposure

Inform patients that accidental exposure (including ingestion), especially by children, may result in respiratory depression or death [see Warnings and Precautions (5.2)]. Instruct patients to take steps to store belladonna and opium suppositories securely and to dispose of unused belladonna and opium suppositories by returning to the pharmacy or delivering to an accredited disposal site.

Interactions with Alcohol and Other CNS Depressants

Inform patients that potentially serious additive effects may occur if belladonna and opium suppositories is used with alcohol or other CNS depressants and not to use such drugs unless supervised by a health care provider [see Warnings and Precautions (5.4), Drug Interactions (7)].

Serotonin Syndrome

Inform patients that belladonna and opium suppositories could cause a rare but potentially life-threatening condition resulting from concomitant administration of serotonergic drugs. Warn patients of the symptoms of serotonin syndrome and to seek medical attention right away if symptoms develop. Instruct patients to inform their physicians if they are taking, or plan to take serotonergic medications. [see Drug Interactions 7].

Adrenal Insufficiency

Inform patients that belladonna and opium suppositories could cause adrenal insufficiency, a potentially life-threatening condition. Adrenal insufficiency may present with non-specific symptoms and signs such as nausea, vomiting, anorexia, fatigue, weakness, dizziness, and low blood pressure. Advise patients to seek medical attention if they experience a constellation of these symptoms [see Warnings and Precautions (5.6)].

Pregnancy

Neonatal Opioid Withdrawal Syndrome

Inform patients that prolonged use of belladonna and opium suppositories during pregnancy can result in neonatal opioid withdrawal syndrome, which may be life-threatening if not recognized and treated [see Warnings and Precautions (5.3), Use in Specific Populations (8.1)].

Embryo-Fetal Toxicity

Inform female patients of reproductive potential that belladonna and opium suppositories can (or may) cause fetal harm and to inform the prescriber of a known or suspected pregnancy [see Use in Specific Populations (8.1)].

Lactation

Advise nursing mothers to monitor infants for increased sleepiness (more than usual), breathing difficulties, or limpness. Instruct nursing mothers to seek immediate medical care if they notice these signs [see Use in Specific Populations (8.2)].

Disposal of Unused Belladonna and Opium Suppositories

Advise patients to return unused suppositories to the pharmacy or deliver to an accredited disposal site.

Medication Guide

Belladonna (bell ah DON ah) and Opium (OH pee um) Suppositories, CII

Belladonna and Opium Suppositories are:

- A strong prescription pain medicine that contains an opioid (narcotic) that is used to manage ureteral spasm pain, when other pain treatments such as non-opioid pain medicines do not treat your pain well enough or you cannot tolerate them.
- An opioid pain medicine that can put you at risk for overdose and death. Even if you take your dose correctly as prescribed you are at risk for opioid addiction, abuse, and misuse that can lead to death.

Important information about Belladonna and Opium Suppositories:

- Get emergency help right away if you take too much belladonna and opium suppositories (overdose). When you first start taking belladonna and opium suppositories, when your dose is changed, or if you take too much (overdose), serious or life-threatening breathing problems that can lead to death may occur.
- Never give anyone else your belladonna and opium suppositories. They could die from taking it. Store belladonna and opium suppositories away from children and in a safe place to prevent stealing or abuse. Selling or giving away belladonna and opium suppositories is against the law.

Do not take Belladonna and Opium Suppositories if you have:

- severe asthma, trouble breathing, or other lung problems.
- a bowel blockage or have narrowing of the stomach or intestines.
- a history of hypersensitivity to belladonna or opium.

Before taking Belladonna and Opium Suppositories, tell your healthcare provider if you have a history of:

- head injury, seizures
- liver, kidney, thyroid problems
- problems urinating
- pancreas or gallbladder problems
- abuse of street or prescription drugs, alcohol addiction, or mental health problems.

Tell your healthcare provider if you are:

- pregnant or planning to become pregnant. Prolonged use of belladonna and opium suppositories during pregnancy can cause withdrawal symptoms in your newborn baby that could be life-threatening if not recognized and treated.
- breastfeeding. Opium passes into breastmilk and may harm your baby.
- taking prescription or over-the-counter medicines, vitamins, or herbal supplements. Taking belladonna and opium suppositories with certain other medicines can cause serious side effects that could lead to death.

When taking Belladonna and Opium Suppositories:

- Do not change your dose. Take belladonna and opium suppositories exactly as prescribed by your healthcare provider. Use the lowest dose possible for the shortest time needed.
- Take your prescribed dose as recommended by the physician. Do not take more than your prescribed dose. If you miss a dose, consult with your healthcare provider.
- Call your healthcare provider if the dose you are taking does not control your pain.
- If you have been taking belladonna and opium suppositories regularly, do not stop taking belladonna and opium suppositories without talking to your healthcare provider.
- After you stop taking belladonna and opium suppositories, return unused suppositories to the pharmacy or deliver to an accredited disposal site.
- Unwrap suppository, then moisten finger and suppository with water before inserting.

While taking Belladonna and Opium Suppositories DO NOT:

- Drive or operate heavy machinery, until you know how belladonna and opium suppositories affects you. Belladonna and opium suppositories can make you sleepy, dizzy, or lightheaded.
- Drink alcohol or use prescription or over-the-counter medicines that contain alcohol. Using products containing alcohol during treatment with belladonna and opium suppositories may cause you to overdose and die.

The possible side effects of Belladonna and Opium Suppositories:

- constipation, nausea, sleepiness, vomiting, tiredness, headache, dizziness, abdominal pain. Call your healthcare provider if you have any of these symptoms and they are severe.

Get emergency medical help if you have:

- trouble breathing, shortness of breath, fast heartbeat, chest pain, swelling of your face, tongue, or throat, extreme drowsiness, light-headedness when changing positions, feeling faint, agitation, high body temperature, trouble walking, stiff muscles, or mental changes such as confusion.

These are not all the possible side effects of belladonna and opium suppositories. Call your doctor for medical advice about side effects. You may report side effects to FDA at 1-800-FDA-1088. For more information go to dailymed.nlm.nih.gov

Manufactured by: Perrigo Minneapolis, MN, www.perrigo.com or call 1-866-634-9120

Issued: 12/2017

PACKAGE LABEL

Belladonna/Opium 16.2/30mg (CII) Supp, #4